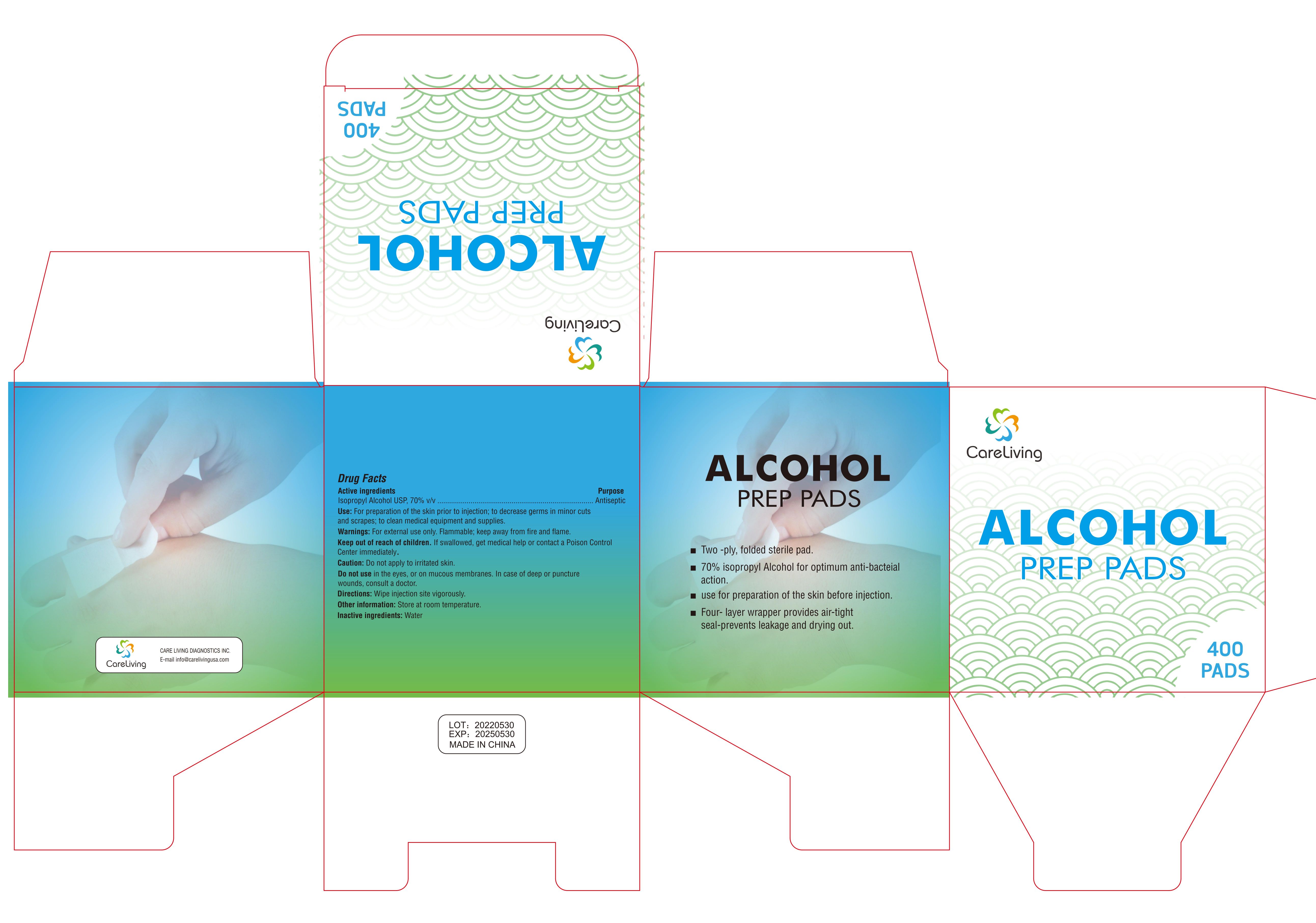 DRUG LABEL: CareLiving Alcohol Prep Pads
NDC: 83568-0001 | Form: SWAB
Manufacturer: CARE LIVING DIAGNOSTICS INC
Category: otc | Type: HUMAN OTC DRUG LABEL
Date: 20230803

ACTIVE INGREDIENTS: ISOPROPYL ALCOHOL 70 mL/100 mL
INACTIVE INGREDIENTS: WATER

Active ingredients

lsopropyl Alcohol USP,70% V/V

Purpose

Antiseptic

Use

- For preparation of the skin prior to injection;
- to decrease germs in minor cuts and scrapes;
- to clean medical equipment and supplies.

Warnings

For external use only. Flammable; keep away from fire and flame.

Keep out of reach of children.

lf swallowed, get medical help or contact a Poison ControCenter immediately.

Caution:

Do not apply to irritated skin.

Do not use

in the eyes, or on mucous membranes ln case of deep or puncturewounds, consult a doctor.

lnactive ingredients:

Water

Manufacture:

CARE LIVING DIAGNOSTICS INC.

Dosage

70ML/100ML